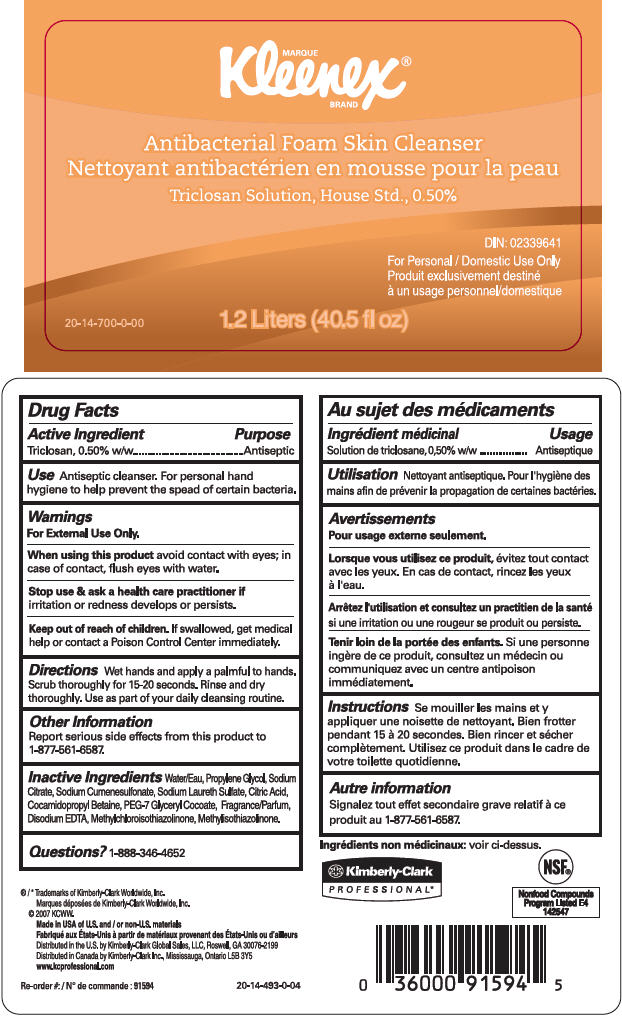 DRUG LABEL: KLEENEX Antibacterial Skin Cleanser
NDC: 55118-565 | Form: SOLUTION
Manufacturer: Kimberly-Clark Corporation
Category: otc | Type: HUMAN OTC DRUG LABEL
Date: 20140929

ACTIVE INGREDIENTS: Triclosan 5 g/1 L
INACTIVE INGREDIENTS: water; Propylene Glycol; Sodium Citrate; Sodium Cumenesulfonate; Sodium Laureth-3 Sulfate; Citric Acid Monohydrate; Cocamidopropyl Betaine; PEG-7 Glyceryl Cocoate; Edetate Disodium; Methylchloroisothiazolinone; Methylisothiazolinone

KLEENEX® Antibacterial Foam Skin Cleanser

Drug Facts

Active Ingredient

Triclosan, 0.50% w/w

Purpose

Antiseptic

Use

Antiseptic cleanser. For personal hand hygiene to help prevent the spead of certain bacteria.

Warnings

For External Use Only.

When using this product avoid contact with eyes; in case of contact, flush eyes with water.

Stop use & ask a health care practitioner if irritation or redness develops or persists.

Keep out of reach of children. If swallowed, get medical help or contact a Poison Control Center immediately.

Directions

Wet hands and apply a palmful to hands. Scrub thoroughly for 15-20 seconds. Rinse and dry thoroughly. Use as part of your daily cleansing routine.

Other Information

Report serious side effects from this product to 1-877-561-6587.

Inactive Ingredients

Water/Eau, Propylene Glycol, Sodium Citrate, Sodium Cumenesulfonate, Sodium Laureth Sulfate, Citric Acid, Cocamidopropyl Betaine, PEG-7 Glyceryl Cocoate, Fragrance/Parfum, Disodium EDTA, Methylchloroisothiazolinone, Methylisothiazolinone.

Questions?

1-888-346-4652

Distributed in the U.S. by Kimberly-Clark Global Sales, LLC, Roswell, GA 30076-2199

Distributed in Canada by Kimberly-Clark Inc., Mississauga, Ontario L5B 3Y5

PRINCIPAL DISPLAY PANEL - 1.2 Liter Container Label

MARQUE
Kleenex®
BRAND

Antibacterial Foam Skin Cleanser

Triclosan Solution, House Std., 0.50%

DIN:02339641
For Personal / Domestic Use Only

1.2 Liters (40.5 fl oz)

20-14-700-0-00